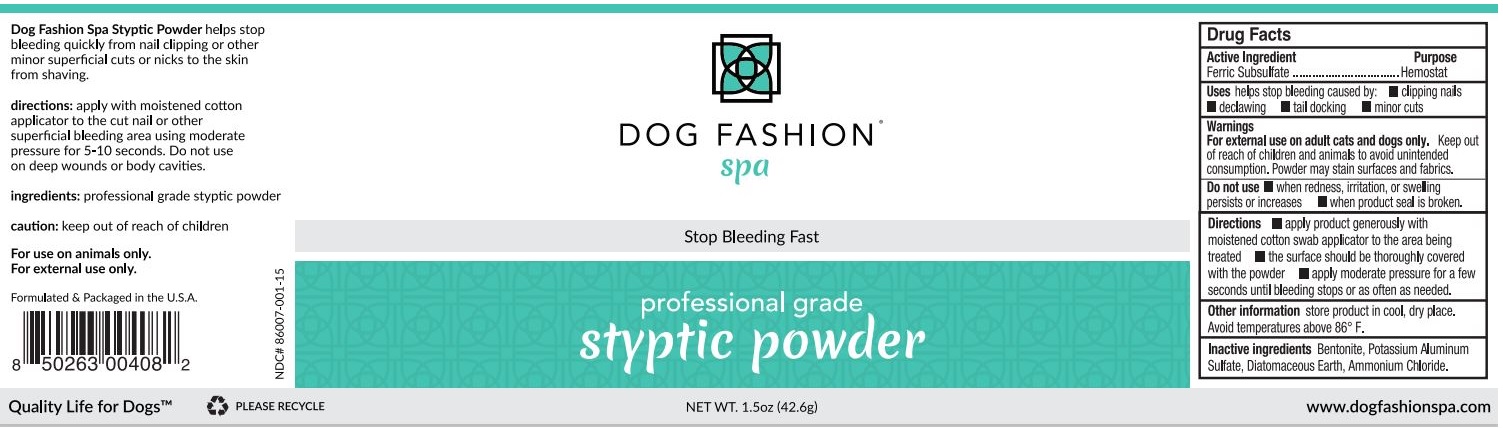 DRUG LABEL: Dog Fashion Spa Styptic
NDC: 86007-001 | Form: POWDER
Manufacturer: Petstore Direct
Category: animal | Type: OTC ANIMAL DRUG LABEL
Date: 20230116

ACTIVE INGREDIENTS: FERRIC SUBSULFATE 35 g/100 g
INACTIVE INGREDIENTS: BENTONITE; POTASSIUM SULFATE; DIATOMACEOUS EARTH; AMMONIUM CHLORIDE

DOG FASHION® spa styptic powder

Active Ingredient

Ferric Subsulfate

Purpose

Hemostat

Uses

helps stop bleeding caused by: • clipping nails • declawing • tail docking • minor cuts

Warnings

For external use on adult cats and dogs only. Keep out of reach of children and animals to avoid unintended consumption. Powder may stain surfaces and fabrics.

Do not use • when redness, irritation, or swelling persists or increases • when product seal is broken.

Directions

• apply product generously with moistened cotton swab applicator to the area being treated • the surface should be thoroughly covered with the powder • apply moderate pressure for a few seconds until bleeding stops or as often as needed.

Other information

store product in cool, dry place. Avoid temperatures above 86º F.

Inactive ingredients

Bentonite, Potassium Aluminum Sulfate, Diatomaceous Earth, Ammonium Chloride.

Stop Bleeding Fast

professional grade

www.dogfashionspa.com

Dog Fashion Spa Styptic Powder helps stop bleeding quickly from nail clipping or other minor superficial cuts or nicks to the skin from shaving.

Do not use on deep wounds or body cavities.

For use on animals only

Formulated & Packaged in the U.S.A.

Quality Life for Dogs™

PLEASE RECYCLE